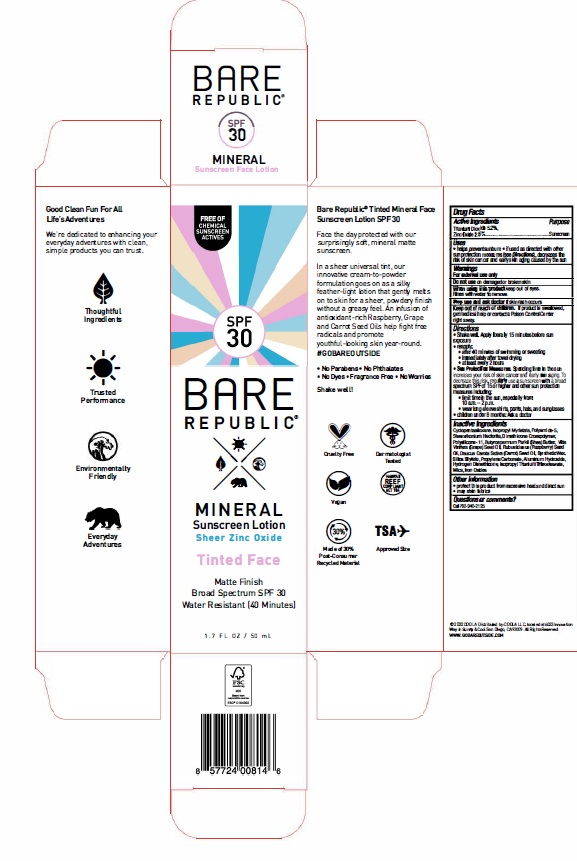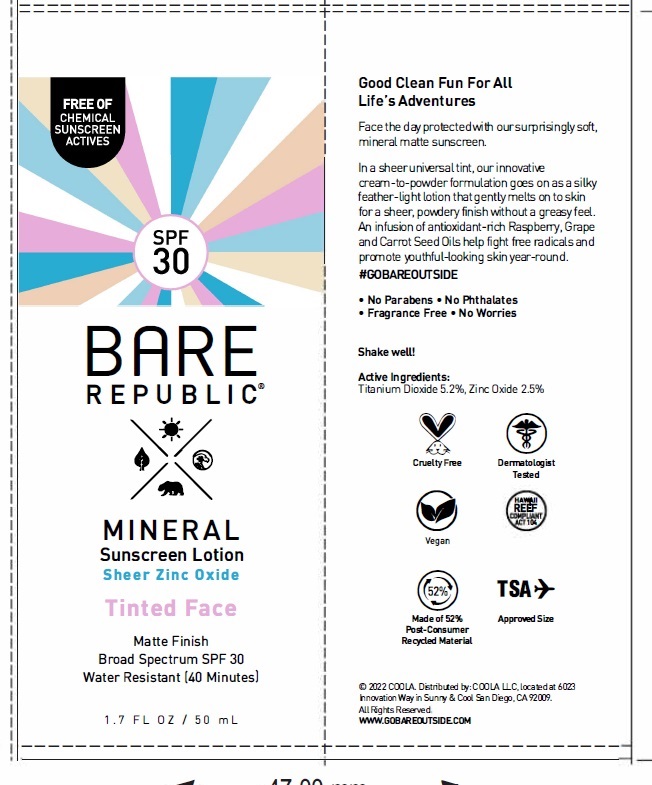 DRUG LABEL: Bare Republic Mineral Matte Tinted Face SPF 30
NDC: 79753-065 | Form: LOTION
Manufacturer: COOLA, LLC
Category: otc | Type: HUMAN OTC DRUG LABEL
Date: 20240522

ACTIVE INGREDIENTS: TITANIUM DIOXIDE 5.2 g/100 mL; ZINC OXIDE 2.5 g/100 mL
INACTIVE INGREDIENTS: DIMETHICONE CROSSPOLYMER (450000 MPA.S AT 12% IN CYCLOPENTASILOXANE); DIMETHICONE/VINYL DIMETHICONE CROSSPOLYMER (SOFT PARTICLE); PROPYLENE CARBONATE; SILICA DIMETHYL SILYLATE; ALUMINUM HYDROXIDE; SHEA BUTTER; CARROT SEED OIL; HYDROGEN DIMETHICONE (13 CST); ISOPROPYL MYRISTATE; POLYAMIDE-5; RASPBERRY SEED OIL; STEARALKONIUM HECTORITE; GRAPE SEED OIL; CYCLOMETHICONE 5; MICA; FERRIC OXIDE RED; SYNTHETIC WAX (1800 MW); FERRIC OXIDE YELLOW; FERROSOFERRIC OXIDE; ISOPROPYL TITANIUM TRIISOSTEARATE

Bare Republic Mineral Matte Tinted Face Lotion SPF 30

ACTIVE INGREDIENT

Titanium Dioxide - 5.2%

Zinc Oxide - 2.5%

PURPOSE

Sunscreen

Uses

- Helps prevent sunburn
- If used as directed with other sun protection measures (see Directions), decreases the risk of skin cancer and early aging caused by the sun

WARNINGS

- For external use only
- Do not use on damaged or broken skin
- When using this product keep out of eyes. Rinse with water to remove.
- Stop use and ask a doctor if rash occurs.

Keep out of reach of children. If product is swallowed, get medical help or contact a Poison Control Center right away.

Directions

- Shake well. Apply liberally 15 minutes before sun exposure.
- Reapply: • after 40 minutes of swimming or sweating • immediately afrer towel drying • at least every 2 hours
- Sun Protection Measures. Spending time in the sun increases your risk of skin cancer and early skin aging. To decrease this risk, regularly use a sunscreen with a broad spectrum SPF of 15 or higher and other sun protection measures including: • limit time in the sun, especially from: 10 a.m. -2 p.m. • wear long-sleeve shirts, pants, hats, and sunglasses
- Children under 6 months: Ask a doctor

INACTIVE INGREDIENT

Cyclopentasiloxane, Isopropyl Myristate, Polyamide-5, Stearalkonium Hectorite, Dimethicone Crosspolymer, Polysilicone-11, Butyrospermum Parkii (Shea) Butter, Vitis Vinifera (Grape) Seed Oil, Rubus Idaeus (Raspberry) Seed Oil, Daucus Carota Sativa (Carrot) Seed Oil, Synthetic Wax, Silica Silylate, Propylene Carbonate, Aluminum Hydroxide, Hydrogen Dimethicone, Isopropyl Titanium Triisostearate, Mica, Iron Oxides

OTHER SAFETY INFORMATION

Protect this product from excessive heat and direct sun

QUESTIONS

Call 760-940-2125